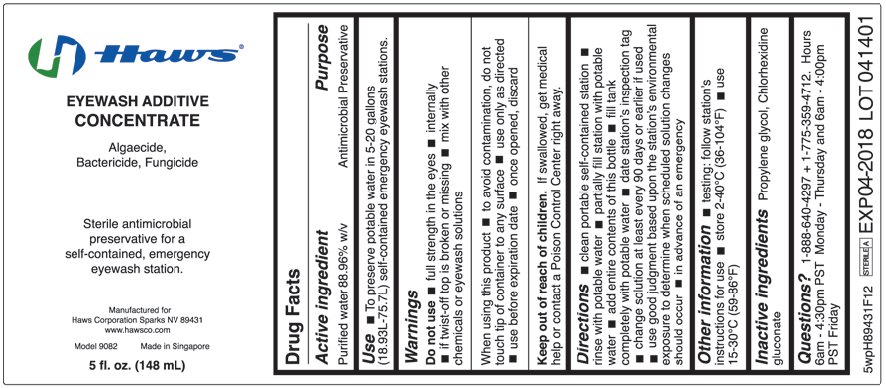 DRUG LABEL: Haws Eyewash Additive
NDC: 66051-210 | Form: SOLUTION, CONCENTRATE
Manufacturer: Haws Corporation
Category: otc | Type: HUMAN OTC DRUG LABEL
Date: 20200121

ACTIVE INGREDIENTS: WATER 889.6 g/1000 mL
INACTIVE INGREDIENTS: CHLORHEXIDINE GLUCONATE; PROPYLENE GLYCOL

Drug Facts

Active ingredient

Purified water 88.96% w/v

Purpose

Antimicrobial Preservative

Use

To preserve potable water in 5-20 gallons (18.93L-75.7L) self-contained emergency eyewash stations.

Warnings

Do not use

- full strength in the eyes
- internally
- if twist-off top is broken or missing
- mix with other chemicals or eyewash solutions

When using this product

- to avoid contamination, do not touch tip of container to any surface
- use only as directed
- use before expiration date
- once opened, discard

Keep out of reach of children. If swallowed, get medical help or contact a Poison Control Center right away.

Directions

- clean portable self-contained station
- rinse with potable water
- partially fill station with potable water
- add entire contents of this bottle
- fill tank completely with potable water
- date station’s inspection tag
- change solution at least every 90 days or earlier if used
- use good judgment based upon the station’s environmental exposure to determine when scheduled solution changes should occur
- in advance of an emergency

Other information

- testing: follow station’s instructions for use
- store 2-40°C (36-104°F)
- use 15-30°C (59-86°F)

Inactive ingredients

Propylene glycol, Chlorhexidine gluconate

Questions?

1-888-640-4297 + 1-775-359-4712. Hours 6am – 4:30pm PST Monday – Thursday and 6am – 4:00pm PST Friday

Package/Label Principal Display Panel

Haws

EYEWASH ADDITIVE CONCENTRATE

Algaecide, Bactericide, Fungicide

Sterile antimicrobial preservative for a self-contained, emergency eyewash station.

Manufactured for
Haws Corporation Sparks NV 89431
www.hawsco.com

Model 9082

Made in Singapore

5 fl. oz. (148 mL)